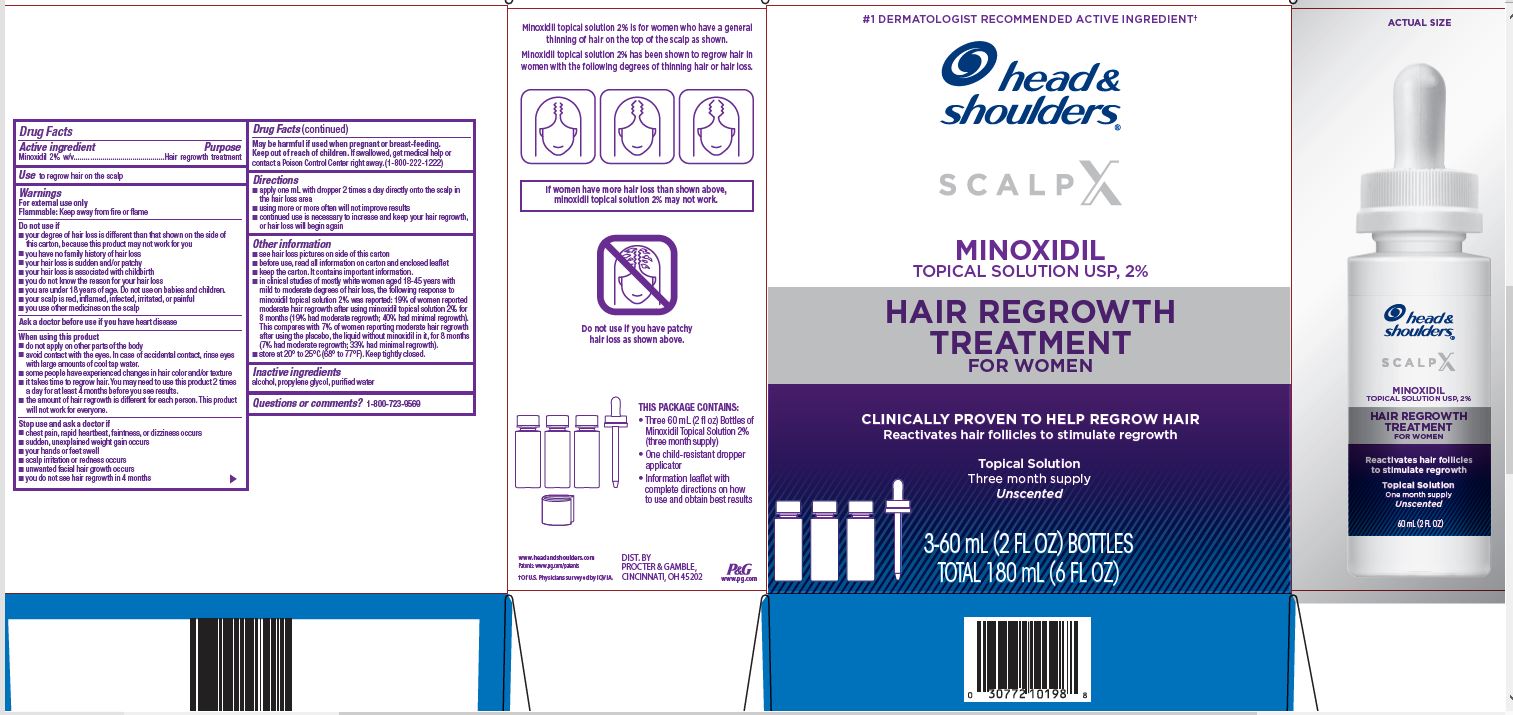 DRUG LABEL: Head and Shoulders Scalp X Minoxidil Hair Regrowth Treatment for Women
NDC: 69423-558 | Form: SOLUTION
Manufacturer: The Procter & Gamble Manufacturing Company
Category: otc | Type: HUMAN OTC DRUG LABEL
Date: 20251231

ACTIVE INGREDIENTS: MINOXIDIL 2 g/100 mL
INACTIVE INGREDIENTS: DEHYDRATED ALCOHOL; WATER; PROPYLENE GLYCOL

Head & Shoulders Scalp X Minoxidil Hair Regrowth Treatment for Women

Drug Facts

Active ingredient

Minoxidil 2% w/v

Purpose

Hair regrowth treatment for women

Use

to regrow hair on the top of the scalp

Warnings

For external use only.

Flammable: Keep away from fire or flame

Do not use if

- your degree of hair loss is different than that shown on side of this carton because this product may not work for you
- you have no family history of hair loss
- your hair loss is sudden and/or patchy
- your hair loss is associated with childbirth
- you do not know the reason for your hair loss
- you are under 18 years of age. Do not use on babies and children
- your scalp is red, inflamed, infected, irritated or painful
- you use other medicines on the scalp

Ask a doctor before use if you have heart disease

When using this product

- do not apply on other parts of the body
- avoid contact with the eyes. In case of accidental contact, rinse eyes with large amounts of cool tap water.
- some people have experienced changes in hair color and/or texture
- it takes time to regrow hair. You may need to use this product 2 times a day for at least 4 months before you see results.
- the amount of hair regrowth is different for each person. This product will not work for allwomen.

Stop use and ask a doctor if

- chest pain, rapid heartbeat, faintness, or dizziness occurs
- sudden, unexplained weight gain occurs
- your hands or feet swell
- scalp irritation or redness occurs
- unwanted facial hair growth occurs
- you do not see hair regrowth in 6 months

PREGNANCY OR BREAST FEEDING

May be harmful if used when pregnant or breast-feeding.

Keep out of reach of children. If swallowed, get medical help or contact a Poison Control Center right away.

(1-800-222-1222)

Directions

- apply one mL with dropper 2 times a day directly onto the scalp in the hair loss area
- using more or more often will not improve results
- continued use is necessary to increase and keep your hair regrowth, or hair loss will begin again

Other information

- see hair loss pictures on side of this carton
- before use, read all information on carton and enclosed leaflet
- keep the carton. It contains important information.
- store at 20-25° C (68-77° F)
- contents under pressure. Do not puncture or incinerate container. Do not expose to heat or store at temperatures above 120°F (49°C).

Inactive ingredients

alcohol,propylene glycol, purified water

Questions or comments?

1-800-723-9569

DIST. BY PROCTER & GAMBLE

CINCINNATI OH 45202.

PRINCIPAL DISPLAY PANEL - Carton

Head & Shoulders

SCALP X

MINOXIDIL

TOPICAL SOLUTION USP, 2%

HAIR REGROWTH

TREATMENT

FOR WOMEN

CLINICALLY PROVEN TO HELP REGROW HAIR

Reactivates hair follicles to stimulate regrowth

Topical Solution

Three month supply

Unscented

3 - 60 mL (2 FL OZ) BOTTLES

TOTAL 180 mL (6 FL OZ)